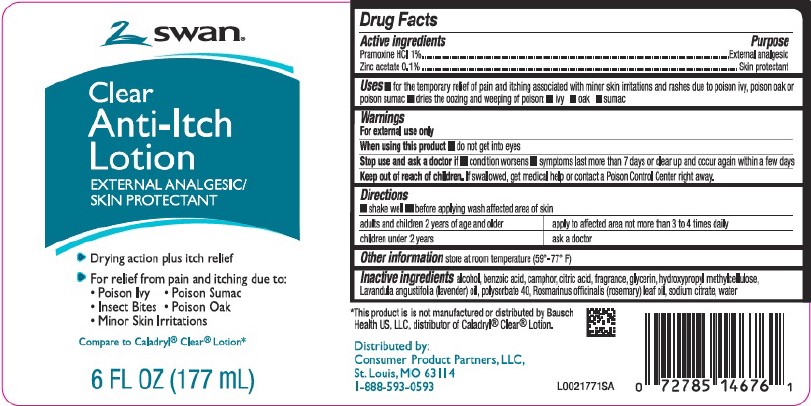 DRUG LABEL: Clear Anti-Itch
NDC: 11344-812 | Form: LOTION
Manufacturer: Consumer Product Partners, LLC
Category: otc | Type: HUMAN OTC DRUG LABEL
Date: 20250616

ACTIVE INGREDIENTS: PRAMOXINE HYDROCHLORIDE 10 mg/1 mL; ZINC ACETATE 1 mg/1 mL
INACTIVE INGREDIENTS: ALCOHOL; BENZOIC ACID; CAMPHOR (SYNTHETIC); CITRIC ACID MONOHYDRATE; GLYCERIN; HYPROMELLOSE, UNSPECIFIED; LAVENDER OIL; POLYSORBATE 40; ROSEMARY OIL; SODIUM CITRATE; WATER

Swan 218.002/218AF
Clear Anti-Itch Lotion

Active ingredients

Pramoxine HCl 1%

Zinc acetate 0.1%

Purpose

External analgesic

Skin protectant

Uses

- for the temporary relief of pain and itching associated with minor skin irritations and rashes due to poison ivy, poison oak or poison sumac
- dries the oozing and weeping of poison: - ivy - oak - sumac

Warnings

For external use only

When using this product

- do not get into eyes

Stop use section and ask a doctor if

- condition worsens
- symptoms last more than 7 days or clear up and occur again within a few days

Keep out of reach of children.

If swallowed, get medical help or contact a Poison Control Center right away.

Directions

- shake well
- before applying wash affected area of skin

adults and children 2 years of age and older - apply to affected area not more than 3 to 4 times daily

children under 2 years - ask a doctor

Other information

store at room temperature (59° - 77°F)

Inactive ingredients

alcohol, benzoic acid, camphor, citric acid, fragrance, glycerin, hydroxypropyl methylcellulose, Lavandula angustifolia (lavender) oil, polysorbate 40, Rosmarinus officinalis (rosemary) leaf oil, sodium citrate, water

Disclaimer

*This product is not manufactured or distributed by Bausch Health US, LLC, distributor of Caladryl® Clear® Lotion.

Adverse reaction

Distributed by:

Consumer Product Partners, LLC,

St. Louis, MO 63114

1-888-593-0593

Principal Display Panel

swan®

Clear Anti-Itch Lotion

External Analgesic/Skin Protectant

Drying action plus itch relief

For relief from pain and itching due to:

- Poison Ivy
- Poison Suman
- Insect Bites
- Poison Oak
- Minor Skin Irritations

Compare to Caladryl® Clear® Lotion*

6 FL OZ (177 mL)